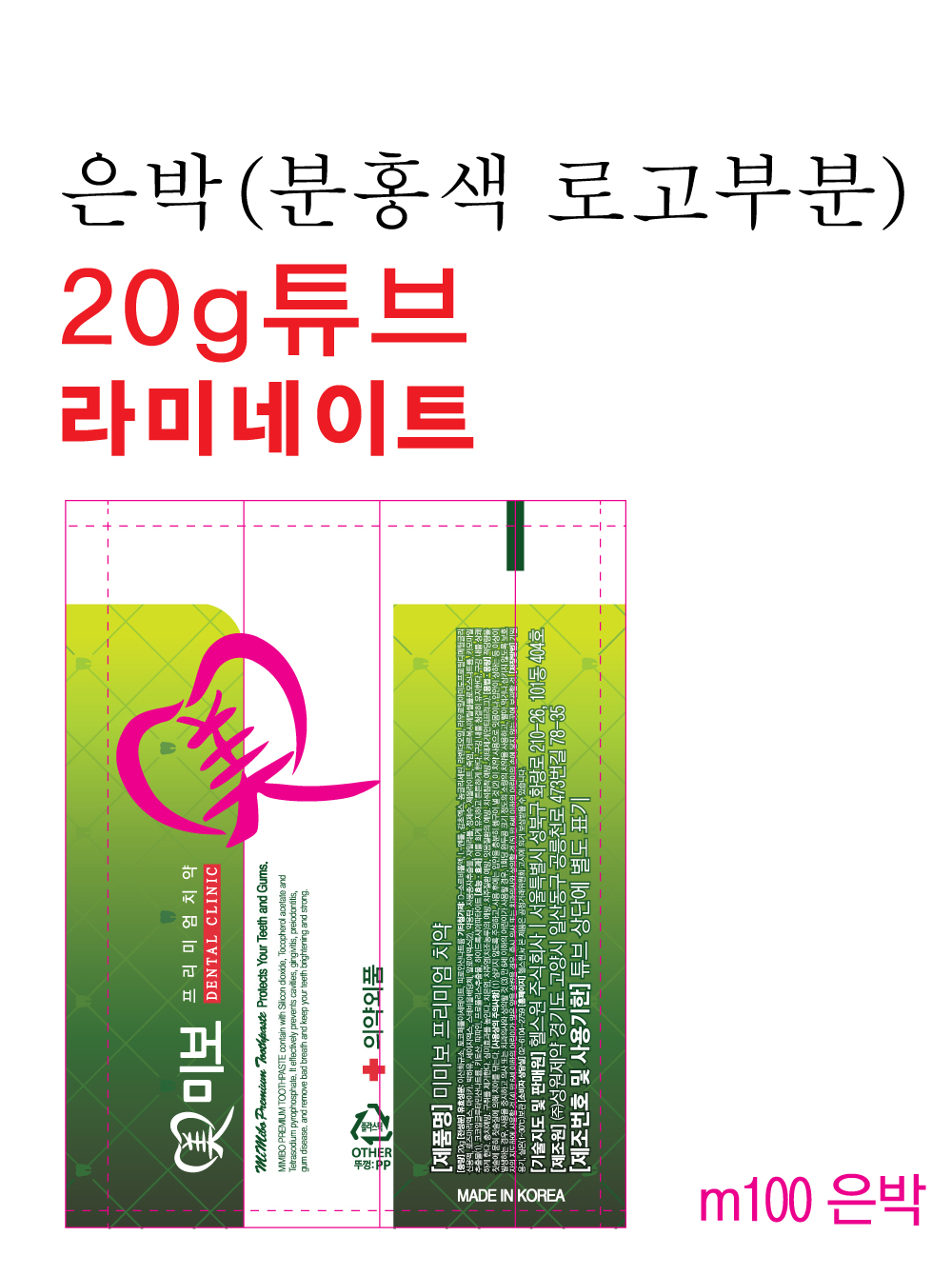 DRUG LABEL: MIMIBO PREMIUM TOOTH
NDC: 73527-0004 | Form: PASTE, DENTIFRICE
Manufacturer: CONE MEDICAL Co., Ltd.
Category: otc | Type: HUMAN OTC DRUG LABEL
Date: 20250102

ACTIVE INGREDIENTS: SILICON DIOXIDE 14 g/100 g; .ALPHA.-TOCOPHEROL ACETATE 0.1 g/100 g; SODIUM PYROPHOSPHATE 0.5 g/100 g
INACTIVE INGREDIENTS: WATER; XYLITOL; LEVOMENTHOL

ACTIVE INGREDIENT

Silicon Dioxide

Tocopherol Acetate

Tetrasodium Pyrophosphate

INACTIVE INGREDIENT

D-Sorbitol Solution

Concentrated Glycerin

Carboxymethylcellulose Sodium

Hydroxyapatite

Medicinal Carbon

Chitosan

Mica

Zeolite

Bamboo Salt

Xylitol

Steviol Glycoside

Papain

Grapefruit Seed Extract

L-Menthol

Mentha Oil

Propolis Extract

Chamomile Extract
Rosemary Extract

Sage Extract

Aloe Extract

Glycyrrhiza Extract

Lavender Oil

Sodium Cocoyl Glutamate

Lauroyl Amidopropyl Dimethyl Glycine Solution

Deionized Water

PURPOSE

For dental care

Keep out of reach of children

INDICATIONS AND USAGE

Apply an appropriate amount to your toothbrush and brush your teeth by brushing.

Warnings

Keep out of reach of children

■ If more than used for rinsing is accidentally swallowed, get medical help or contact a Poison Control Center right away.

Other Information

■ Store in an airtight container at room temperature

■ Date of use : 36 months from the date of manufacture

DOSAGE AND ADMINISTRATION

For dental use only